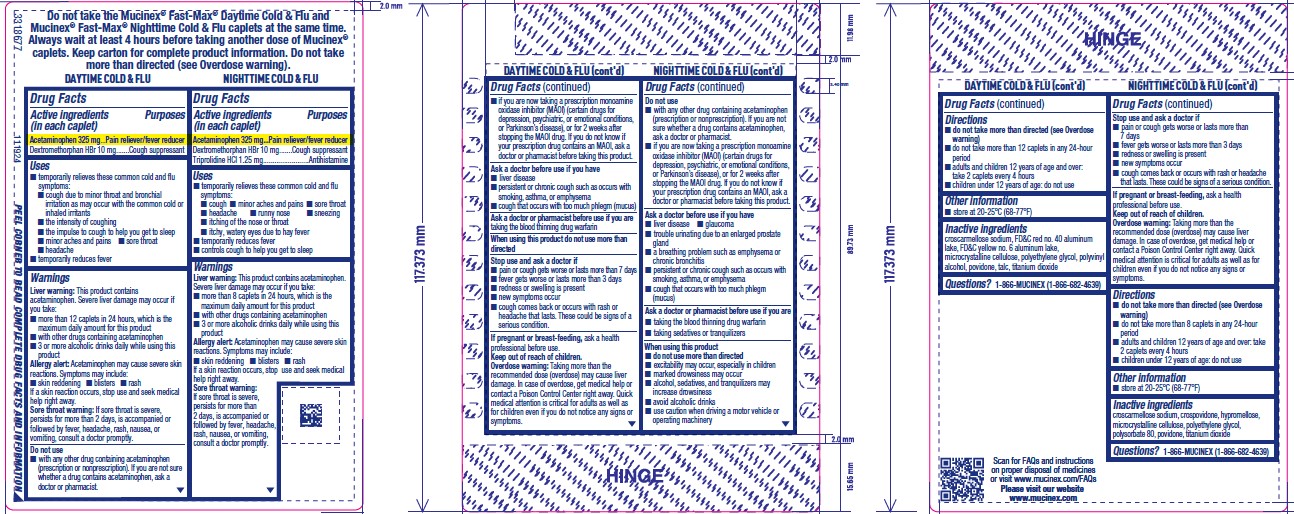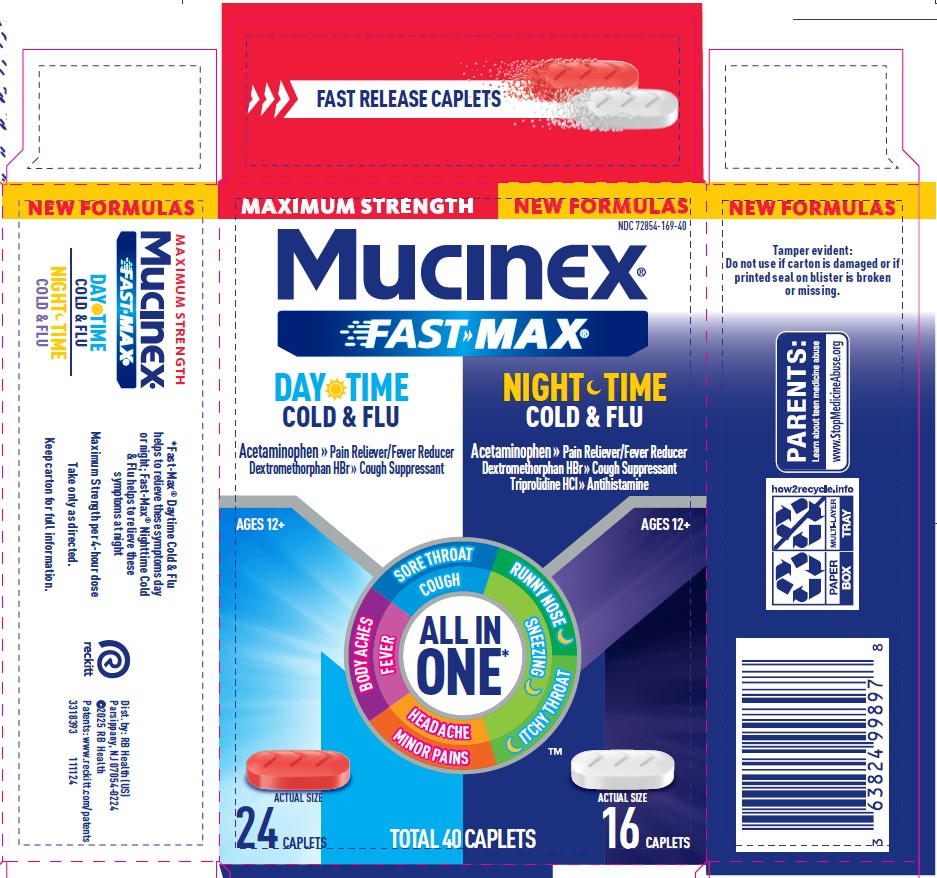 DRUG LABEL: Mucinex Fast-Max Day Cold and Flu and Mucinex Nightshift Night Severe Cold and Flu
NDC: 72854-169 | Form: KIT | Route: ORAL
Manufacturer: RB Health (US) LLC
Category: otc | Type: HUMAN OTC DRUG LABEL
Date: 20250410

ACTIVE INGREDIENTS: ACETAMINOPHEN 325 mg/1 1; DEXTROMETHORPHAN HYDROBROMIDE 10 mg/1 1; ACETAMINOPHEN 325 mg/1 1; DEXTROMETHORPHAN HYDROBROMIDE 10 mg/1 1; TRIPROLIDINE HYDROCHLORIDE 1.25 mg/1 1
INACTIVE INGREDIENTS: CROSCARMELLOSE SODIUM; CROSPOVIDONE; FD&C RED NO. 40; FD&C YELLOW NO. 6; ALUMINUM OXIDE; MAGNESIUM STEARATE; MICROCRYSTALLINE CELLULOSE; POLYETHYLENE GLYCOL, UNSPECIFIED; POLYVINYL ALCOHOL, UNSPECIFIED; POVIDONE, UNSPECIFIED; TALC; TITANIUM DIOXIDE; CROSCARMELLOSE SODIUM; CROSPOVIDONE; FERRIC OXIDE RED; HYDROXYPROPYL CELLULOSE, UNSPECIFIED; MICA; MICROCRYSTALLINE CELLULOSE; POLYVINYL ALCOHOL, UNSPECIFIED; POLYVINYL ALCOHOL GRAFT POLYETHYLENE GLYCOL COPOLYMER (3:1; 45000 MW); POVIDONE, UNSPECIFIED; SILICON DIOXIDE; STEARIC ACID; TALC; TITANIUM DIOXIDE

MUCINEX® FAST-MAX® Daytime Cold & Flu & Nighttime Cold & Flu Caplets

Drug Facts

ACTIVE INGREDIENT

Daytime Cold & Flu

Acetaminophen 325 mg
Dextromethorphan HBr 10 mg

Mucinex Nighttime Cold & Flu
Acetaminophen 325 mg
Dextromethorphan HBr 10 mg
Triprolidine HCl 1.25 mg

PURPOSE

Active ingredients (in each caplet) Mucinex Fast-Max Day Cold & Flu | Purposes
Acetaminophen 325 mg | Pain reliever/fever reducer
Dextromethorphan HBr 10 mg | Cough suppressant

Active ingredients (in each caplet) Mucinex Nightshift Night Severe Cold & Flu | Purposes
Acetaminophen 325 mg | Pain reliever/fever reducer
Dextromethorphan HBr 10 mg | Cough suppressant
Triprolidine HCl 1.25 mg | Antihistamine

Uses

Mucinex Fast-Max Day Cold & Flu

- temporarily relieves these common cold and flu symptoms:
  - cough
  - nasal congestion
  - minor aches and pains
  - sore throat
  - headache
  - stuffy nose
  - sinus congestion and pressure
- temporarily reduces fever
- helps loosen phlegm (mucus) and thin bronchial secretions to rid the bronchial passageways of bothersome mucus and make coughs more productive

Mucinex Nightshift Night Severe Cold & Flu

- temporarily relieves these common cold and flu symptoms:
  - cough
  - nasal congestion
  - minor aches and pains
  - sore throat
  - headache
  - sneezing
  - sinus congestion and pressure
  - runny nose
  - itching of the nose or throat
  - itchy, watery eyes due to hay fever
- temporarily reduces fever
- controls cough to help you get to sleep

Warnings

Liver warning

This product contains acetaminophen.

Severe liver damage may occur if you take:

- more than 4,000 mg in 24 hours, which is the maximum daily amount
- with other drugs containing acetaminophen
- 3 or more alcoholic drinks daily while using this product

Allergy alert

Acetaminophen may cause severe skin reactions.

Symptoms may include:

- skin reddening
- blisters
- rash

If a skin reaction occurs, stop use and seek medical help right away.

Sore throat warning

If sore throat is severe, persists for more than 2 days, is accompanied or followed by fever, headache, rash, nausea, or vomiting, consult a doctor promptly.

Do not use

- with any other drug containing acetaminophen (prescription or nonprescription). If you are not sure whether a drug contains acetaminophen, ask a doctor or pharmacist.
- if you are now taking a prescription monoamine oxidase inhibitor (MAOI) (certain drugs for depression, psychiatric, or emotional conditions, or Parkinson's disease), or for 2 weeks after stopping the MAOI drug. If you do not know if your prescription drug contains an MAOI, ask a doctor or pharmacist before taking this product.

Ask a doctor before use if you have

- liver disease
- heart disease
- diabetes
- high blood pressure
- thyroid disease
- glaucoma (Nightshift Night Severe Cold & Flu only)
- trouble urinating due to an enlarged prostate gland
- a breathing problem such as emphysema or chronic bronchitis (Nightshift Night Severe Cold & Flu only)
- persistent or chronic cough such as occurs with smoking, asthma, chronic bronchitis, or emphysema
- cough that occurs with too much phlegm (mucus)

Ask a doctor or pharmacist before use if you are

- taking the blood thinning drug warfarin
- taking sedatives or tranquilizers (Nightshift Night Severe Cold & Flu only)

When using this product

- do not use more than directed
- excitability may occur, especially in children (Nightshift Night Severe Cold & Flu only)
- marked drowsiness may occur (Nightshift Night Severe Cold & Flu only)
- alcohol, sedatives, and tranquilizers may increase drowsiness (Nightshift Night Severe Cold & Flu only)
- avoid alcoholic drinks (Nightshift Night Severe Cold & Flu only)
- use caution when driving a motor vehicle or operating machinery (Nightshift Night Severe Cold & Flu only)

Stop use and ask a doctor if

- nervousness, dizziness, or sleeplessness occur
- pain, nasal congestion, or cough gets worse or lasts more than 7 days
- fever gets worse or lasts more than 3 days
- redness or swelling is present
- new symptoms occur
- cough comes back, or occurs with fever, rash, or headache that lasts. These could be signs of a serious condition.

PREGNANCY OR BREAST FEEDING

If pregnant or breast-feeding, ask a health professional before use.

Keep out of reach of children.

Overdose warning

Taking more than the recommended dose (overdose) may cause liver damage. In case of overdose, get medical help or contact a Poison Control Center right away. Quick medical attention is critical for adults as well as for children even if you do not notice any signs or symptoms.

Directions

Mucinex Fast-Max Day Cold & Flu

- do not take more than directed (see Overdose warning)
- do not take more than 12 caplets in any 24-hour period
- adults and children 12 years of age and over: take 2 caplets every 4 hours
- children under 12 years of age: do not use

Mucinex Nightshift Night Severe Cold & Flu

- do not take more than directed (see Overdose warning)
- do not take more than 8 caplets in any 24-hour period
- adults and children 12 years of age and over: take 2 caplets every 4 hours
- children under 12 years of age: do not use

Other information

- store at 20-25°C (68-77°F)

Inactive ingredients Mucinex Fast-Max Day Cold & Flu

croscarmellose sodium, crospovidone, FD&C red no. 40 aluminum lake, FD&C yellow no. 6 aluminum lake, magnesium stearate, microcrystalline cellulose, polyethylene glycol, polyvinyl alcohol, povidone, talc, titanium dioxide

Inactive ingredients Mucinex Nightshift Night Severe Cold & Flu

croscarmellose sodium, crospovidone, ferric oxide, hydroxypropyl cellulose, mica, microcrystalline cellulose, polyvinyl alcohol, polyvinyl alcohol polyethylene glycol copolymer, povidone, silicon dioxide, stearic acid, talc, titanium dioxide

Questions?

1-866-MUCINEX (1-866-682-4639) You may also report side effects to this phone number.

Dist. by: RB Health (US)
Parsippany, NJ 07054-0224

PRINCIPAL DISPLAY PANEL - Kit Carton

NDC 72854-169